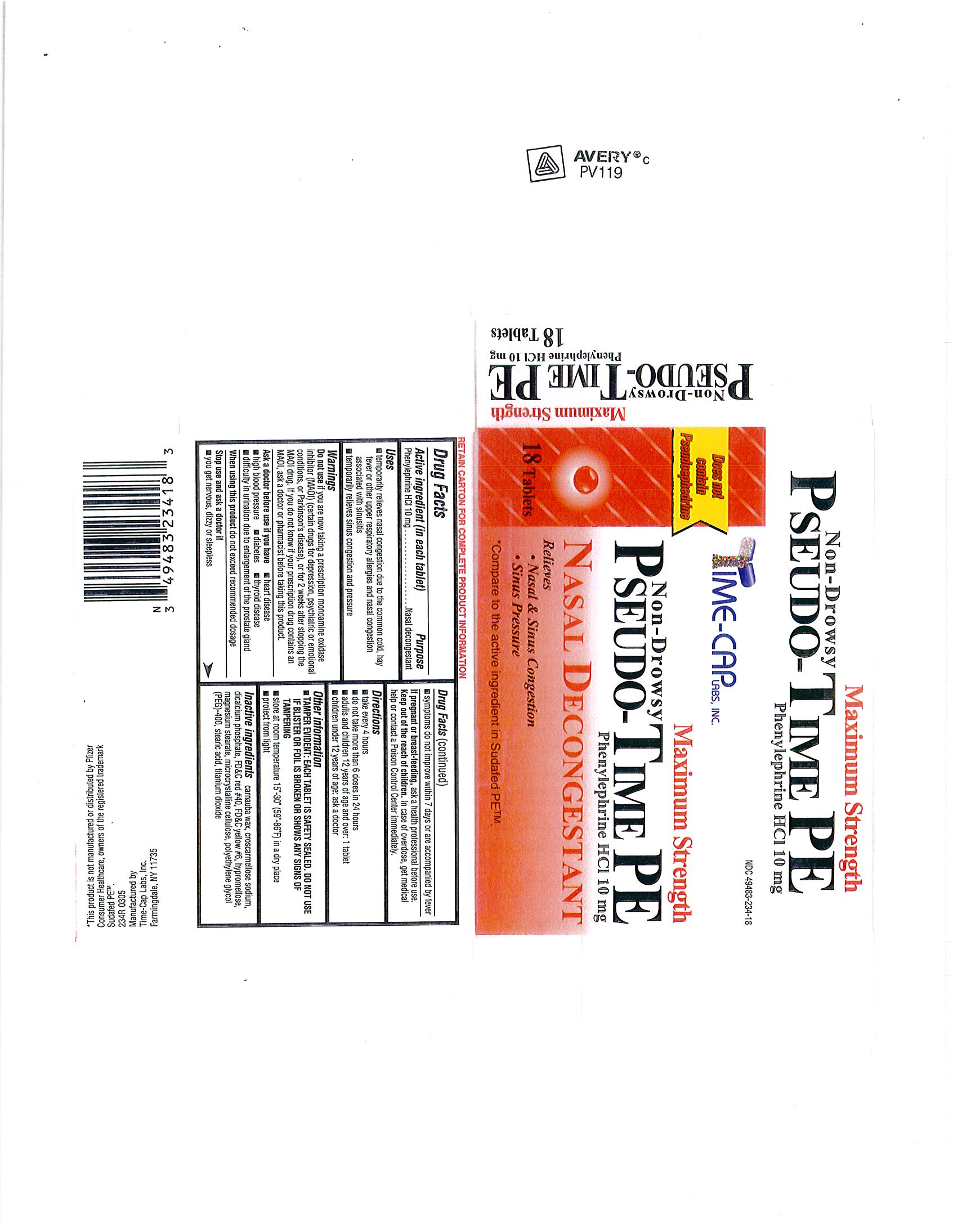 DRUG LABEL: PSEUDO TIME PE
NDC: 49483-234 | Form: TABLET, FILM COATED
Manufacturer: TIME CAP LABORATORIES, INC.
Category: otc | Type: HUMAN OTC DRUG LABEL
Date: 20181214

ACTIVE INGREDIENTS: PHENYLEPHRINE HYDROCHLORIDE 10 mg/1 1
INACTIVE INGREDIENTS: CARNAUBA WAX; CROSCARMELLOSE SODIUM; DIBASIC CALCIUM PHOSPHATE DIHYDRATE; FD&C RED NO. 40; FD&C YELLOW NO. 6; HYPROMELLOSES; MAGNESIUM SILICATE; CELLULOSE, MICROCRYSTALLINE; POLYETHYLENE GLYCOL 400; STEARIC ACID; TITANIUM DIOXIDE

49483-234 pseudo time pe

ACTIVE INGREDIENT

Each tablet contains: Phenylephrine HCl 10 mg

INACTIVE INGREDIENT

INACTIVE INGREDIENTS: CARNAUBA WAX, CROSCARMELLOSE SODIUM, DIBASIC CALCIUM PHOSPHATE DIHYDRATE, FD-C RED#40 ALUMINUM LAKE, FD-C YELLOW#6 ALUMINUM LAKE, HYPROMELLOSE, MAGNESIUM STEARATE, MICROCRYSTALLINE CELLULOSE, POLYETHYLENE GLYCOL (PEG) 400, STEARIC ACID, TITANIUM DIOXIDE

KEEP OUT OF REACH OF CHILDREN

keep out of the reach of children. In case of overdose, get medical help or contact a Poison Control Center immediately.

PURPOSE: nasal decongestant

Uses:

Temporarily relieves nasal congestion due to the common cold, hay fever or other upper respiratory allergies and nasal congestion associated with sinusitis

Temporarily relieves sinus congestion and pressure

DIRECTIONS:

Take every 4 hours; Do not take more than 6 doses in 24 hours; Adults and children 12 years of age and over; 1 tablet

Children under 12 years of age; ask a doctor

WARNINGS;

Do not use if you are taking a prescription monoamine oxidase inhibitor (MAOI) (certain drugs for depression, psychiatric or emotional conditions, or Parkinson's disease) or for 2 weeks after stopping the MAOI drug. If you do not know if your prescription drug contains an MAOI, ask a doctor or pharmacist before taking this product.